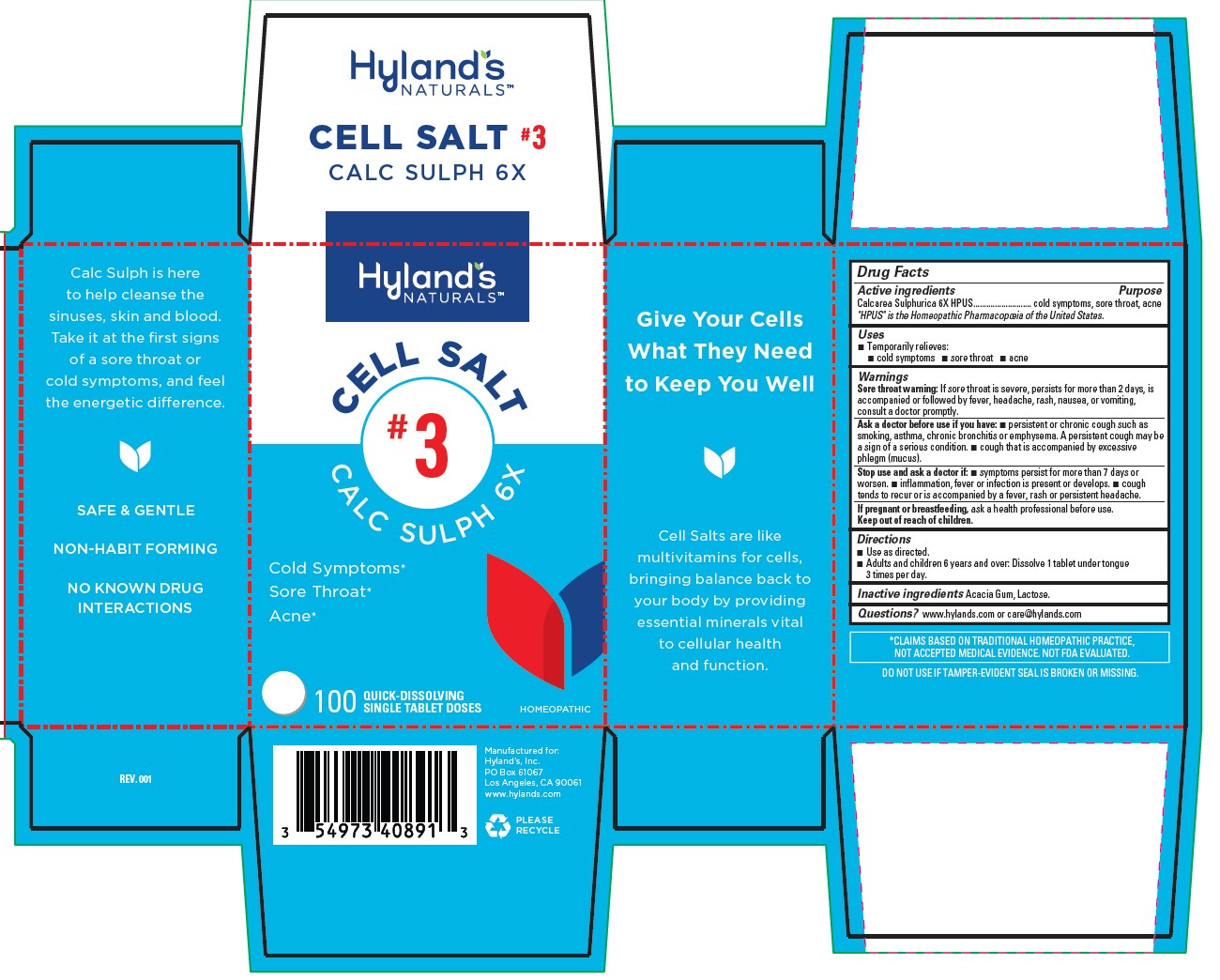 DRUG LABEL: CALC SULPH 6X
NDC: 54973-4089 | Form: TABLET, SOLUBLE
Manufacturer: Hyland's Inc.
Category: homeopathic | Type: HUMAN OTC DRUG LABEL
Date: 20221207

ACTIVE INGREDIENTS: CALCIUM SULFATE ANHYDROUS 6 [hp_X]/1 1
INACTIVE INGREDIENTS: LACTOSE MONOHYDRATE; ACACIA

Cell Salt #3 Calc Sulph 6X

PURPOSE

Cold Symptoms

Sore Throat

Acne

Drug Facts

Active ingredients | Purpose
Calcarea Sulphurica 6X HPUS | cold symptoms, sore throat, acne

HPUS" is the Homeopathic Pharmacopoeia of the United States.

Uses

■Temporarily relieves:
■ cold symptoms ■ sore throat ■ acne

Warnings

Sore Throat Warning

If sore throat is severe, persists for more than 2 days, is accompanied or followed by fever, headache, rash, nausea, or vomiting,
consult a doctor promptly.

Ask a doctor before use if you have

■ persistent or chronic cough such as smoking, asthma, chronic bronchitis or emphysema. A persistent cough may be a sign of a serious condition. ■ cough that is accompanied by excessive phlegm (mucus).

Stop use and ask a doctor if

■ symptoms persist for more than 7 days or worsen. ■ inflammation, fever or infection is present or develops. ■ cough tends to recur or is accompanied by a fever, rash or persistent headache.

If pregnant or breastfeeding

Ask a health professional before use.

Directions

■ Use as directed.
■ Adults and children 6 years and over: Dissolve 1 tablet under tongue 3 times per day.

Inactive ingredients

Acacia Gum, Lactose.

Questions?

www.hylands.com or care@hylands.com

PACKAGE LABEL - 100 TABLETS BOTTLE CARTON

Hyland's

NATURALS™

CELL SALT

#3

CALC SULPH 6X

Cold Symptoms*

Sore Throat*

Acne*

100

QUICK-DISSOLVING

SINGLE TABLET DOSES

HOMEOPATHIC